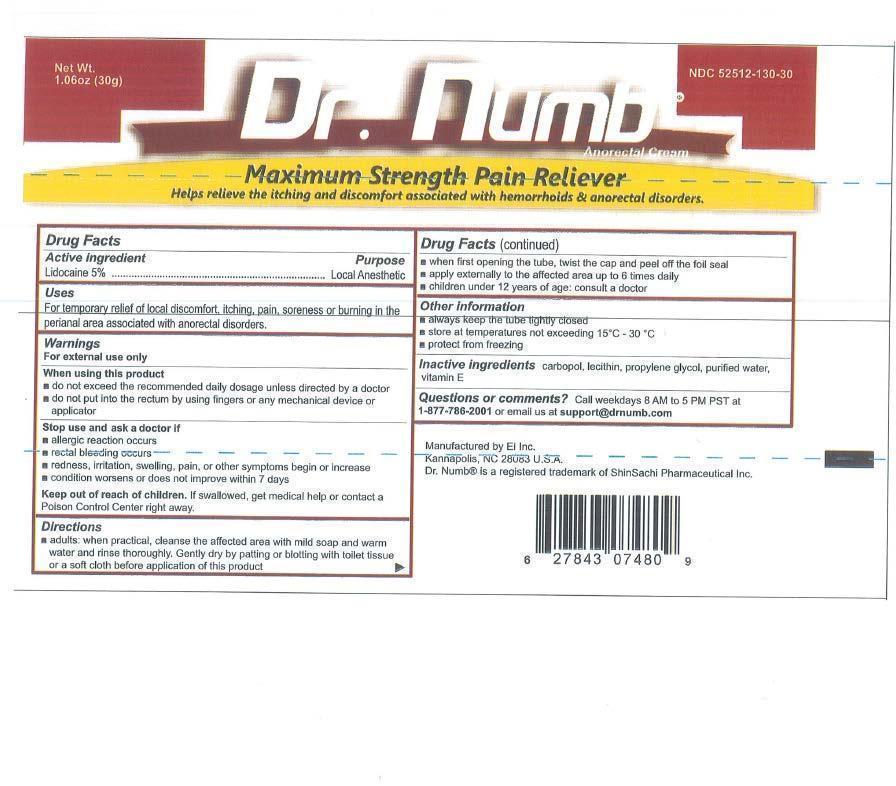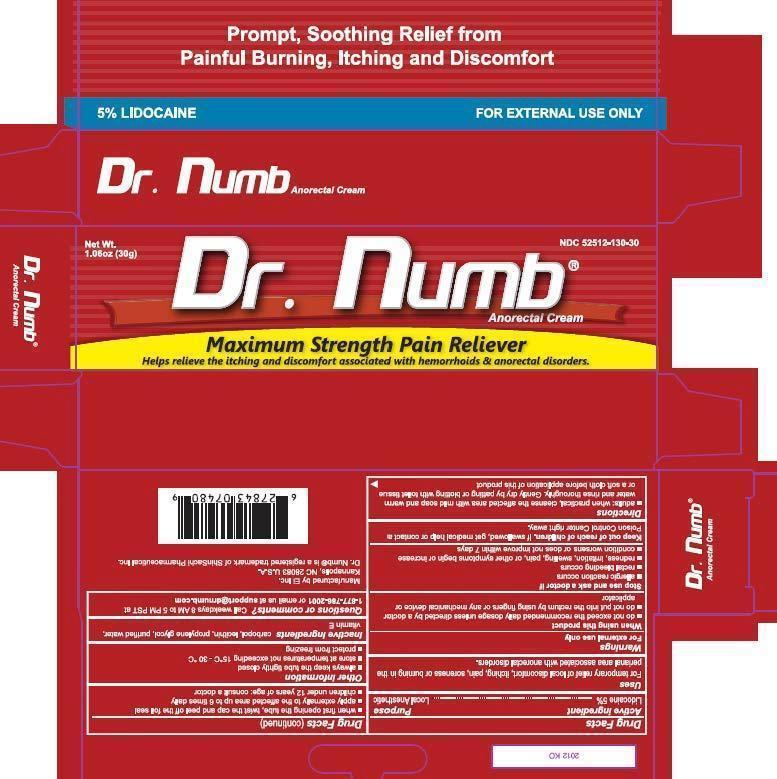 DRUG LABEL: Dr. Numb
NDC: 52512-130 | Form: CREAM
Manufacturer: Ei Inc.
Category: otc | Type: HUMAN OTC DRUG LABEL
Date: 20121207

ACTIVE INGREDIENTS: Lidocaine 5 g/100 g
INACTIVE INGREDIENTS: Propylene Glycol; Benzyl Alcohol; .ALPHA.-TOCOPHEROL ACETATE; LECITHIN, SOYBEAN; CARBOMER HOMOPOLYMER TYPE B

Dr. Numb Anorectal Cream

Acive Ingredients Purpose

Lidocaine 5% Local Anesthetic

Uses

For temprary relief of local discomfort, itching pain, soreness or burning in the perianal area associated with anorectal disorders.For temprary relief of local discomfort, itching pain, soreness or burning in the perianal area associated with anorectal disorders.

Keep out of reach of children

If swallowed, get medical help or contact a Poison Control Center right away.

INDICATIONS AND USAGE

For temporary relief of local discomfort, itching, pain, soreness or burning in the perianal area assosiated with anorectal disorders.

Warnings

For external use only

When using this product

- do not exceed the recommended daily dosage unless directed by a doctor
- do not put into the rectum by using fingers or any mechanical device or applicator

Stop use and ask a doctor if

- allergic reaction occurs
- redness, irritation, swelling, pain, or other simptoms begin or increase
- condition worsens or does not improve withing 7 days

Directions

- adults: when practical, cleanse the affected area with mild soap and warm water and rinse thoroughly. Gently dry by patting or blotting with toilet tissue or soft cloth before application of this product
- when first opening the tube, twist the cap and peel off the foil seal
- apply externally to the affected area up to 6 times daily
- children under 12 years of age: consult a doctor

Inactive ingredients

Carbopol, lecithin, propylene glycol, purified water, vitamin E.

Other information

- always keep the tube tightly closed
- store at temperatures not exceeding 15^0C- 30^0C
- protect from freezing

Questions and comments?

Call weekdays 8 a.m. to 5 p.m. PST at 8-877-786-2001 oe email us at support@drnumb.com